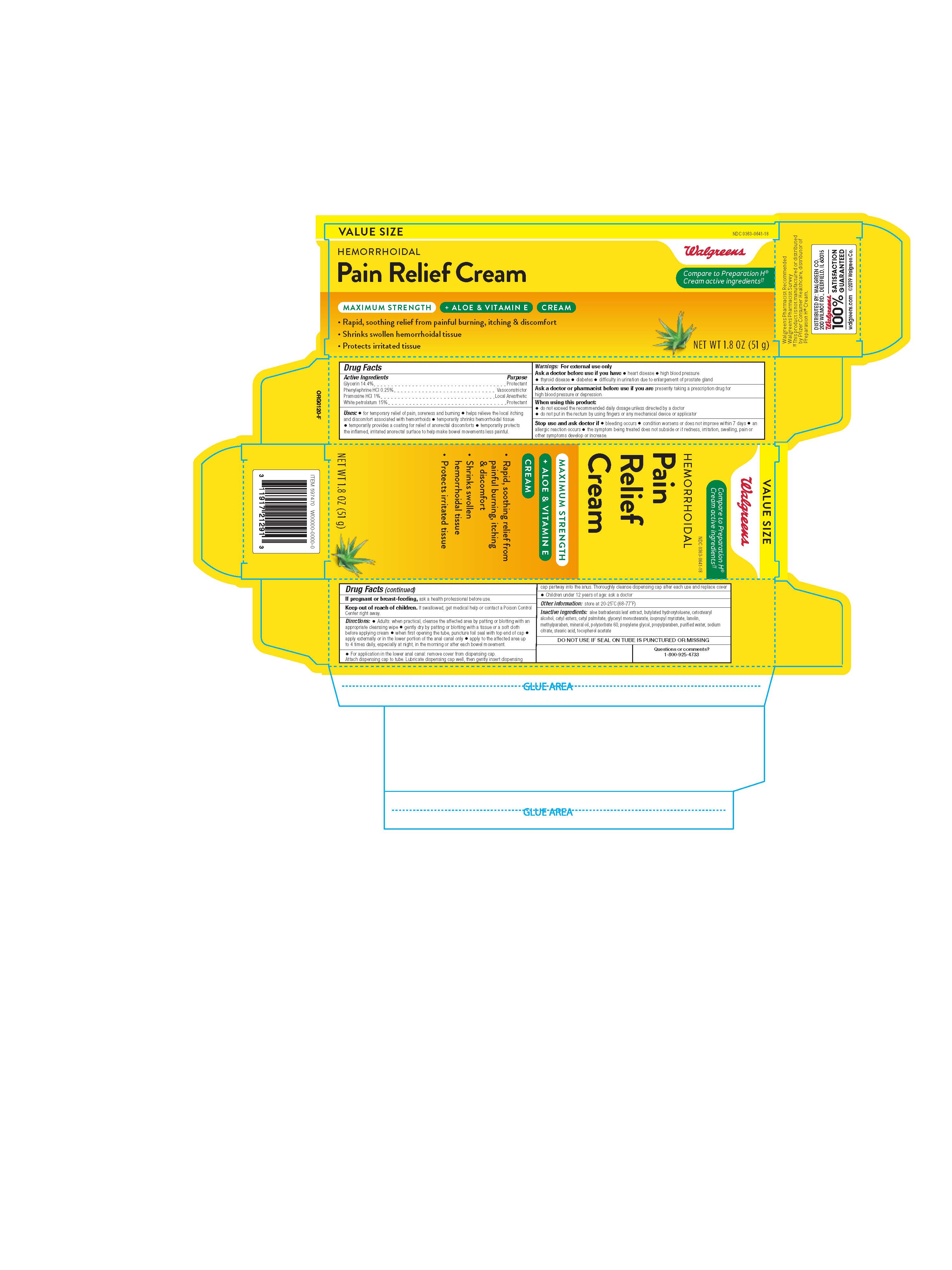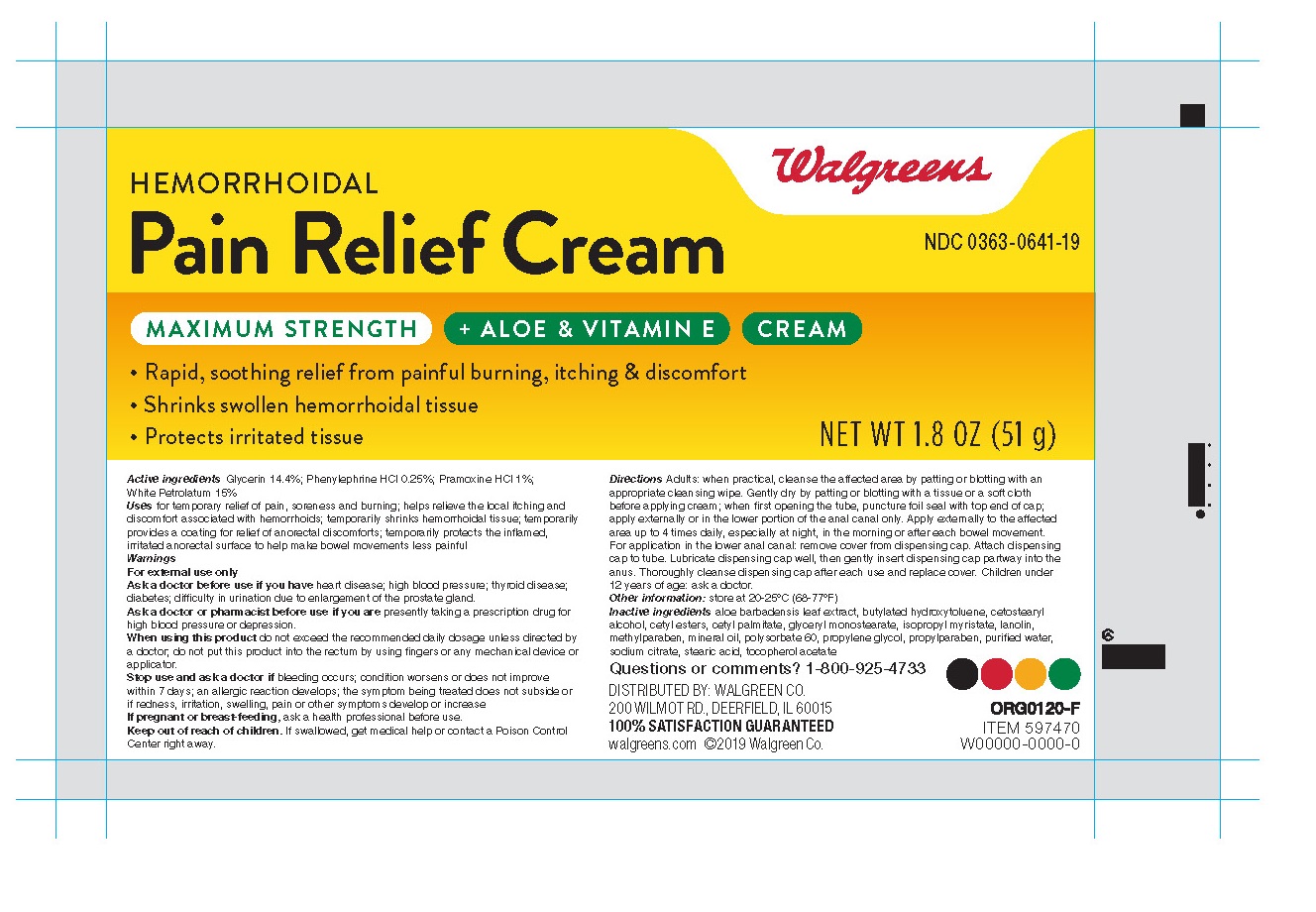 DRUG LABEL: Hemorrhoidal Cream
NDC: 0363-0641 | Form: CREAM
Manufacturer: Walgreens
Category: otc | Type: HUMAN OTC DRUG LABEL
Date: 20260115

ACTIVE INGREDIENTS: PETROLATUM 150 mg/1 g; GLYCERIN 144 mg/1 g; PRAMOXINE HYDROCHLORIDE 10 mg/1 g; PHENYLEPHRINE HYDROCHLORIDE 2.5 mg/1 g
INACTIVE INGREDIENTS: WATER; POLYSORBATE 60; PROPYLENE GLYCOL; STEARYL ALCOHOL; GLYCERYL MONOSTEARATE; MINERAL OIL; CETYL PALMITATE; ALOE; SODIUM CITRATE; ISOPROPYL MYRISTATE; STEARIC ACID; LANOLIN; METHYLPARABEN; PROPYLPARABEN

Walgreens®Hemorrhoidal M/S Cream 1.8oz

Active Ingredients

Glycerin 14.4%

Phenylephrine HCL 0.25%

Pramoxine HCl 1%

White petrolatum 15%

Purpose

Protectant

Vasoconstrictor

Local anasthetic

Protectant

Uses

-for temporary relief of pain, soreness, and burning.

-helps relieve the local itching and discomfort associated with hemorrhoids.

-temporarily shrinks hemorrhoidal tissue.

-temporarily provides a coating for relief of anorectal discomforts.

-temporarily protects the inflamed, irritated anorectal surface to help make bowel movements less painful.

Warnings

For external use only.

Ask a doctor before use if you have

-heart disease

-high blood pressure

-thyroid disease

-diabetes

-difficulty in urination due to enlargement of the prostate gland

Ask a doctor or pharmacist before use if you are

presently taking a prescription drug for high blood pressure or depression.

When using this product

-do not exceed the recommended daily dosage unless directed by a doctor

-do not put into the rectum by using fingers or any mechanical device or applicator

Stop use and ask a doctor if

-bleeding occurs

-condition worsens or does not improve within 7 days

-an allergic reaction develops

-the symptom being treated does not subside or if redness, irritation, swelling pain, or other symptoms develop or increase

If pregnant or breast-feeding

ask a health professional before use.

Keep out of reach of children.

If swallowed, get medical help or contact a Poison Control Center right away.

Directions

-adults: when practical, cleanse the affected area by patting or blotting with an appropriate cleansing wipe. Gently dry by patting or blotting with a tissue or a soft cloth before applying cream. When first opening the tube, puncture foil seal with top end of cap. Apply externally or in the lower portion of the anal canal only. Apply to the affected area up to 4 times daily, especially at night, in the morning or after each bowel movement.

-For application in the lower anal canal: remove cover from dispensing cap. Attach dispensing cap to tube. Lubrcate dispensing cap well, then gently insert dispensing cap partway into the anus.

-thoroughly cleanse dispensing cap after each use and replace cover.

-children under 12 years of age: ask a doctor.

Directions

Apply externally or in the lower portion of the anal canal only. Apply to the affected area up to 4 times daily, especially at night, in the morning or after each bowel movement.

-For application in the lower anal canal: remove cover from dispensing cap. Attach dispensing cap to tube. Lubrcate dispensing cap well, then gently insert dispensing cap partway into the anus.

Other information

store at 20-25oC (68-77oF)

Inactive ingredients

Aloe barbadensis leaf extract, butylated hydroxytoluene, cetyl esters, cetyl palmitate, glyceryl monostearate, isopropyl myristate, lanolin, methylparaben, mineral oil, polysorbate 60, propylene glycol, propylparaben, sodium citrate, stearic acid, stearyl alcohol, vitamin E, water